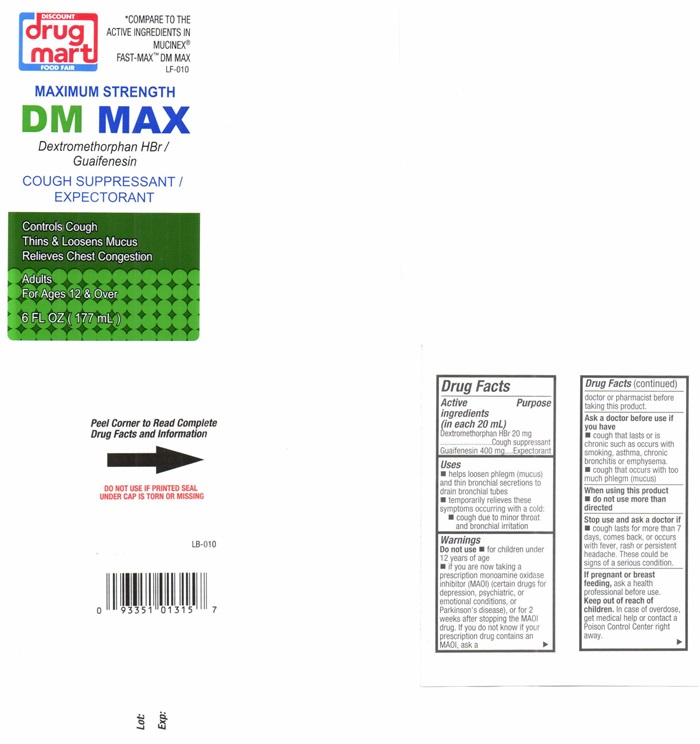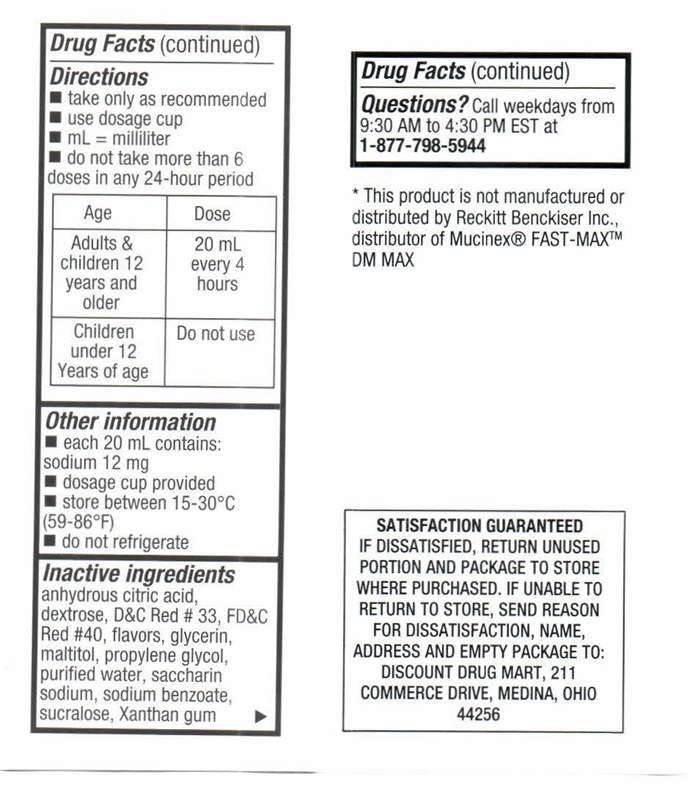 DRUG LABEL: MAXIUM STRENGTH DM MAX
NDC: 53943-518 | Form: LIQUID
Manufacturer: Discount Drug Mart
Category: otc | Type: HUMAN OTC DRUG LABEL
Date: 20251219

ACTIVE INGREDIENTS: DEXTROMETHORPHAN HYDROBROMIDE 20 mg/20 mL; GUAIFENESIN 400 mg/20 mL
INACTIVE INGREDIENTS: ANHYDROUS CITRIC ACID; DEXTROSE; D&C RED NO. 33; FD&C RED NO. 40; GLYCERIN; MALTITOL; PROPYLENE GLYCOL; WATER; SACCHARIN SODIUM; SODIUM BENZOATE; SUCRALOSE; XANTHAN GUM

Drug Facts Active ingredients (in each 20 mL)

Dextromethorphan HBr, USP 20 mg

Guaifenesin 400 mg

Purpose

Cough Suppressant

Expectorant

Keep out of reach of children.In case of overdose, get medical help or contact a Poison Control Center right away.

Uses

- helps loosen phlegm (mucus) and thin bronchial secretions to drain bronchial tubes
- temporaroly relieves these symptoms occuring with a cold:
- cough due to minor throat and bronchial irritation

Warning

DO NOT USE IF PRINTED SEAL UNDER CAP IS TORN OR MISSING.

Do not use

- for children under 12 years of age
- if you are now taking a prescription monoamine oxidase inhibitor (MAOI) (certain drugs for depression, psychiatric or emotional conditions or Parkinson's disease), or for 2 weeks after stopping the MAOI drug. If you do not know if your prescription drug contains an MAOI, ask a doctor or pharmacist before taking this product.

Ask a doctor before use if you have

- cough that lasts or is chronic such as occurs with smoking, asthma, chronic bronchitis or emphysema
- cough that occurs with too much phlegm (mucus)

When using this product

- do not use more than directed

Stop use and ask a doctor if

- cough lasts for more than 7 days, comes back, or occurs with fever, rash or persistant headache. These could be signs of a serious condition.

If pregnany or breast feeding,

ask a health professional before use.

Directions

- take only as recommended
- use dosage cup
- mL= millilter
- do not take more than 6 doses in any 24-hour period

Age | Dose
Adults & children 12 years adn older | 20 mL every 4 hours
Children under 12 years of age | Do not use

Other information

- each 20 mL contains: sodium 12 mg
- dosage cup provided
- store between 15-30°C (59-86°F)
- do not refrigerate

Inactive ingredients

anhydrous citric acid, dextrose, D&C Red # 33, FD&C Red # 40, flavors, glycerin, maltitol, propylene glycol, purified water, saccharin sodium, sodium benzoate, sucralose, Xanthan gum

Questions?

Call weekdays from 9:30 AM to 4:30 PM EST at 1-877-798-5944

DISCOUNT drug mart FOOD FAIR MAXIUM STRENGTH DM MAX product label

*COMPARE TO THE ACTIVE INGREDIENTS IN MUCINEX® FAST-MAX™-DM MAX

LF-010

DISCOUNT

drug mart

FOOD FAIR

MAXIUM STRENGTH DM MAX

Dextromethorphan HBr/ Guaifenesin

COUGH SUPPRESSANT/

EXPECTORANT

Controls Cough

Thins & Loosens mucus

Relieves Chest Congestion

Adults

For Ages 12 & Over

6 FL OZ (177 mL)

* This product is not manufactured or distributed by Reckitt Benckiser Inc., distributor of MUCINEX® FAST-MAX™ DM MAX

LB - 010 LOT: EXP:

Peel Corner to Read Complete Drug Facts and Information

SATISFACTION GUARANTEED
IF DISSASIFIED , RETURN UNUSED PORTION AND PACKAGE TO STORE WHERE PURCHASED. IF UNABLE TO RETURN TO STORE, SEND REASON FOR DISSATISFACTION, NAME, ADDRESS AND EMPTY PACKAGE TO: DISCOUNT DRUG MART, 211 COMMERCE DRIVE, MEDINA, OHIO 44256

res